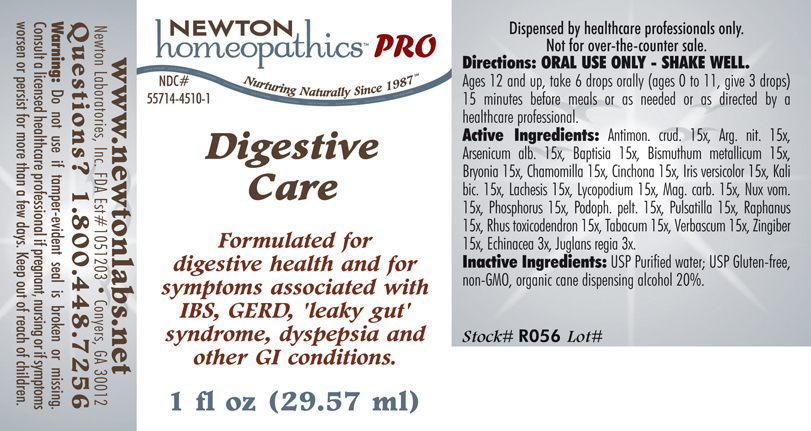 DRUG LABEL: Digestive Care 
NDC: 55714-4510 | Form: LIQUID
Manufacturer: Newton Laboratories, Inc.
Category: homeopathic | Type: HUMAN PRESCRIPTION DRUG LABEL
Date: 20110601

ACTIVE INGREDIENTS: Antimony Trisulfide 15 [hp_X]/1 mL; Silver Nitrate 15 [hp_X]/1 mL; Arsenic Trioxide 15 [hp_X]/1 mL; Baptisia Tinctoria Root 15 [hp_X]/1 mL; Bismuth 15 [hp_X]/1 mL; Bryonia Alba Root 15 [hp_X]/1 mL; Matricaria Recutita 15 [hp_X]/1 mL; Cinchona Officinalis Bark 15 [hp_X]/1 mL; Iris Versicolor Root 15 [hp_X]/1 mL; Potassium Dichromate 15 [hp_X]/1 mL; Lachesis Muta Venom 15 [hp_X]/1 mL; Lycopodium Clavatum Spore 15 [hp_X]/1 mL; Magnesium Carbonate 15 [hp_X]/1 mL; Strychnos Nux-vomica Seed 15 [hp_X]/1 mL; Phosphorus 15 [hp_X]/1 mL; Podophyllum 15 [hp_X]/1 mL; Pulsatilla Vulgaris 15 [hp_X]/1 mL; Daikon 15 [hp_X]/1 mL; Toxicodendron Pubescens Leaf 15 [hp_X]/1 mL; Tobacco Leaf 15 [hp_X]/1 mL; Verbascum Thapsus 15 [hp_X]/1 mL; Ginger 15 [hp_X]/1 mL; Echinacea, Unspecified 3 [hp_X]/1 mL; Juglans Regia Fruit Rind, Immature 3 [hp_X]/1 mL
INACTIVE INGREDIENTS: Alcohol

Digestive Care

INDICATIONS & USAGE SECTION

Digestive Care Formulated for digestive health and for symptoms associated with IBS, GERD, 'leaky gut' syndrome, dyspepsia and other GI conditions.

DOSAGE & ADMINISTRATION SECTION

Directions: ORAL USE ONLY - SHAKE WELL. Ages 12 and up, take 6 drops orally (ages 0 to 11, give 3 drops) 15 minutes before meals or as needed or as directed by a healthcare professional.

ACTIVE INGREDIENT SECTION

Antimon. crud. 15x, Arg. nit. 15x, Arsenicum alb. 15x, Baptisia 15x, Bismuthum metallicum 15x, Bryonia 15x, Chamomilla 15x, Cinchona 15x, Iris versicolor 15x, Kali bic. 15x, Lachesis 15x, Lycopodium 15x, Mag. carb. 15x, Nux vom.15x, Phosphorus 15x, Podoph. pelt. 15x, Pulsatilla 15x, Raphanus 15x, Rhus toxicodendron 15x, Tabacum 15x, Verbascum 15x, Zingiber 15x, Echinacea 3x, Juglans regia 3x.

PURPOSE SECTION

Formulated for digestive health and for symptoms associated with IBS, GERD, 'leaky gut' syndrome, dyspepsia and other GI conditions.

INACTIVE INGREDIENT SECTION

Inactive Ingredients: USP Purified Water; USP Gluten-free, non-GMO, organic cane dispensing alcohol 20%.

QUESTIONS? SECTION

www.newtonlabs.net Newton Laboratories, Inc. FDA Est # 1051203 - Conyers, GA 30012
Questions? 1.800.448.7256

WARNINGS SECTION

Warning: Do not use if tamper - evident seal is broken or missing. Consult a licensed healthcare professional if pregnant, nursing or if symptoms worsen or persist for more than a few days. Keep out of reach of children.

PREGNANCY OR BREAST FEEDING SECTION

Consult a licensed healthcare professional if pregnant, nursing or if symptoms worsen or persist for more than a few days.

KEEP OUT OF REACH OF CHILDREN SECTION

Keep out of reach of children.